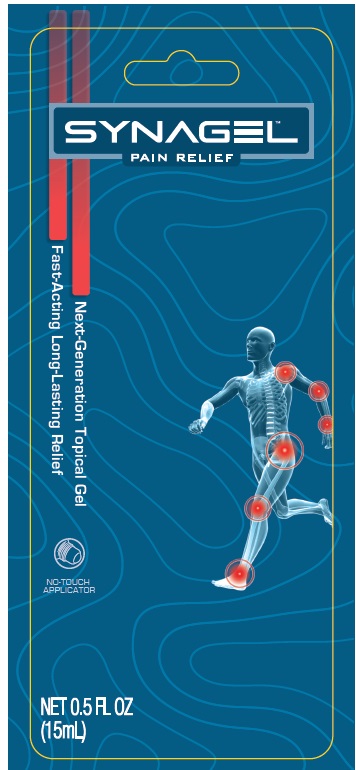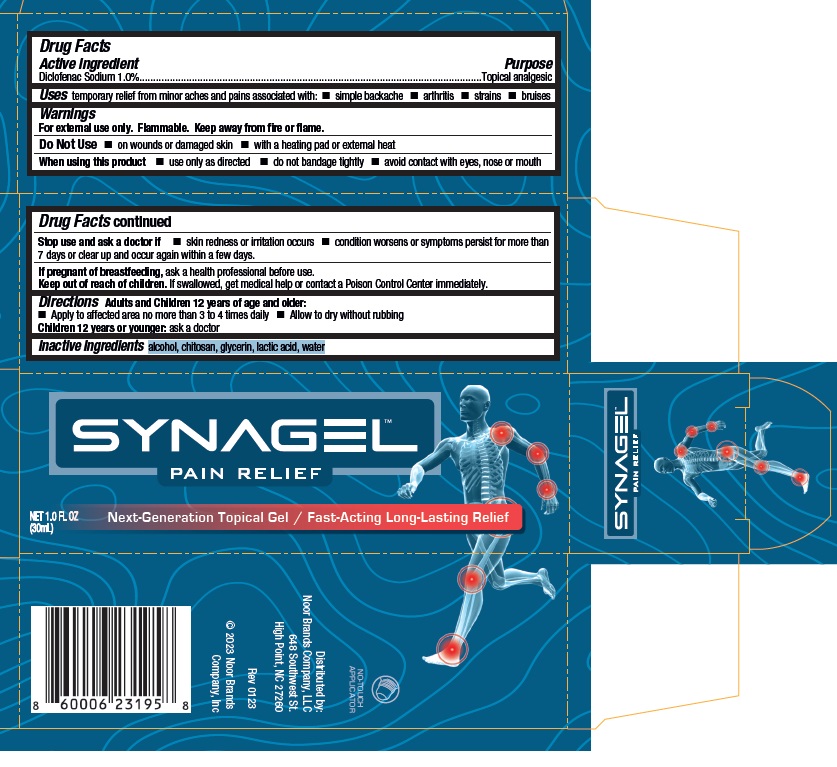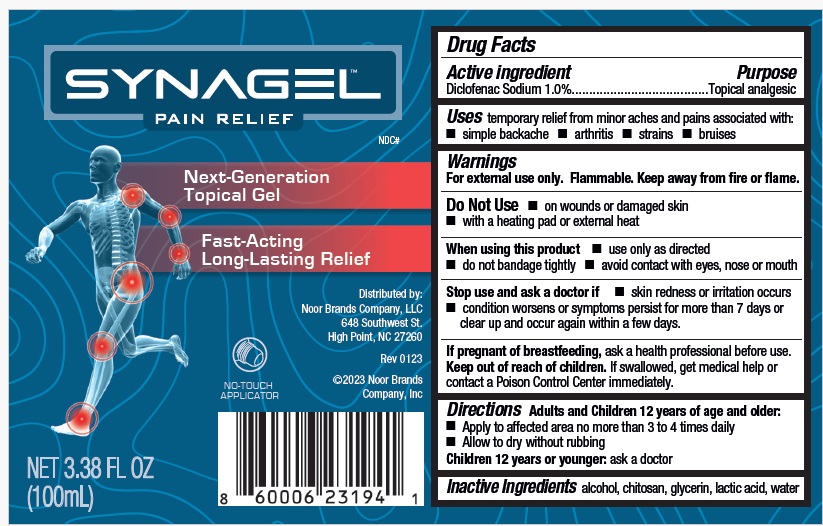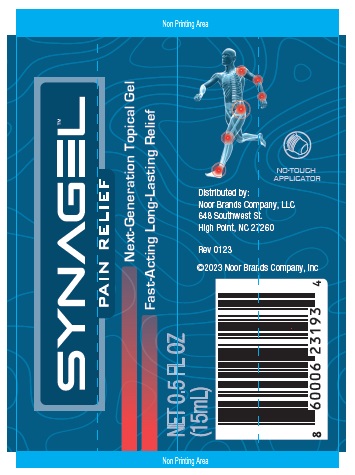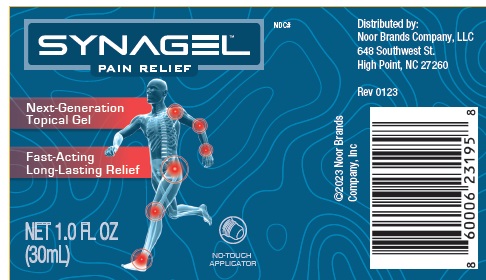 DRUG LABEL: SynaGel
NDC: 82213-002 | Form: GEL
Manufacturer: Noor Brands Company, LLC
Category: otc | Type: HUMAN OTC DRUG LABEL
Date: 20231103

ACTIVE INGREDIENTS: DICLOFENAC SODIUM 1 g/100 mL
INACTIVE INGREDIENTS: ALCOHOL; POLIGLUSAM; GLYCERIN; LACTIC ACID; WATER

Active ingredient.

Diclofenac Sodium 1.0%

Purpose

Topical analgesic

Uses

- temporary relief from minor aches and pains associated with:
- simple backache
- arthritis
- strains
- bruises

Warnings

For external use only. Flammable. Keep away from fire or flame.

Do Not Use

- on wounds or damaged skin
- with a heating pad or external heat

When using this product

- use only as directed
- do not bandage tightly
- avoid contact with eyes, nose or mouth

Stop use and ask a doctor if

- skin redness or irritation occurs
- condition worsens or symptoms persist for more than 7 days or clear up and occur again within a few days.

If pregnant of breastfeeding, ask a health professional before use.

Keep out of reach of children. If swallowed, get medical help or contact a Poison Control Center immediately.

Directions

Adults and Children 12 years of age and older:

- Apply to affected area no more than 3 to 4 times daily
- Allow to dry without rubbing

Children 12 years or younger: ask a doctor

Inactive ingredients

alcohol, chitosan, glycerin, lactic acid, water